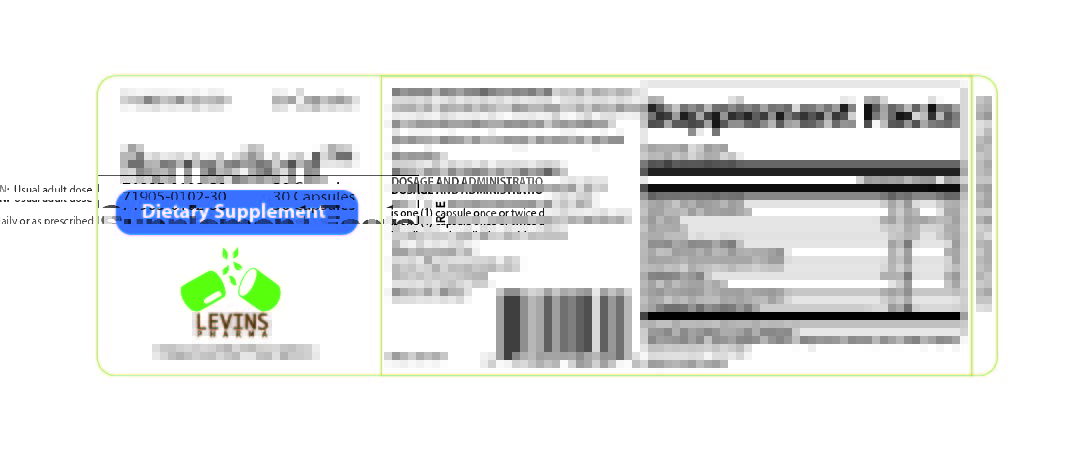 DRUG LABEL: Remedient
NDC: 71905-102 | Form: CAPSULE
Manufacturer: Levins Pharmaceuticals, LLC
Category: other | Type: Dietary Supplement
Date: 20190719

ACTIVE INGREDIENTS: ASCORBIC ACID 200 mg/1 1; Vitamin D 20 ug/1 1; FOLIC ACID 1667 ug/1 1; CYANOCOBALAMIN 6 ug/1 1; CALCIUM CITRATE 40 mg/1 1; IRON PROTEIN SUCCINYLATE 3.6 mg/1 1; MAGNESIUM GLYCINATE 8.5 mg/1 1; MAGNESIUM OXIDE 60.3 mg/1 1; ZINC 8 mg/1 1; POLAPREZINC 37.5 mg/1 1; CARNOSINE 28 mg/1 1

Remedient™

STATEMENT OF IDENTITY

Remedient™ Capsules Dietary Supplement

HEALTH CLAIM

Dispensed by Prescription†

Acid-lowering medications can increase pH in the stomach and small intestine, leading to decreased absorption of key vitamins and minerals. Remedient™ is an orally administered prescription vitamin formulation designed to replete these key vitamins and minerals and help support gastro-esophageal health. ††

†This product is a prescription- folic acid with or without other dietary ingredients that – due to increased folic acid levels increased risk associated with masking of B12
deficiency (pernicious anemia) requires administration under the care of a licensed medical practitioner (61 FR 8760). The most appropriate way to ensure pedigree
reporting consistent with these regulatory guidelines and safety monitoring is to dispense this product only by prescription (Rx). This is not an Orange Book product.
This product may be administered only under a physician’s supervision and all prescriptions using this product shall be pursuant to state statutes as applicable. The
ingredients, indication or claims of this product are not to be construed to be drug claims.

1. Federal Register Notice of August 2, 1973 (38 FR 20750

2. Federal Register Notice of October 17, 1980 (45 FR 69043, 69044)

3. Federal Register Notice of March 5, 1996 (61 FR 8760)

†† These statements have not been evaluated by the Food and Drug Administration. This product is not intended to diagnose, treat, cure or prevent any disease.

WARNINGS

This product is contraindicated in patients with a known hypersensitivity to any of the ingredients.

PRECAUTIONS

Remedient™ capsules should only be used under the direction and supervision of a licensed medical practitioner. Use with caution in patients that may have a medical condition, are pregnant, lactating, trying to conceive, under the age of 18, or taking medications.

DOSAGE AND ADMINISTRATION

Usual adult dose is one (1) capsule once or twice daily or as prescribed by a licensed medical practitioner. Remedient™ should be taken on an empty stomach for optimal absorption.

Remedient™ capsules are supplied as (purple and white, oblong-shaped) capsules in a child-resistant bottle of 30-count ("71905-0102-30"**).

**Levins Pharmaceuticals does not represent these product codes to be National Drug Codes (NDC). Product codes are formatted according to standard industry practice, to meet the formatting requirement by pedigree reporting and supply-chain control including pharmacies.

SAFE HANDLING WARNING

Store at 20°-25°C (68°-77°F); excursions permitted to 15°-30°C (59°-86°F) [See USP Controlled Room Temperature.]

KEEP OUT OF REACH OF CHILDREN

Tamper evident: Do not use if seal is broken or missing

To report adverse events or to obtain product information, contact 228-392-0043.